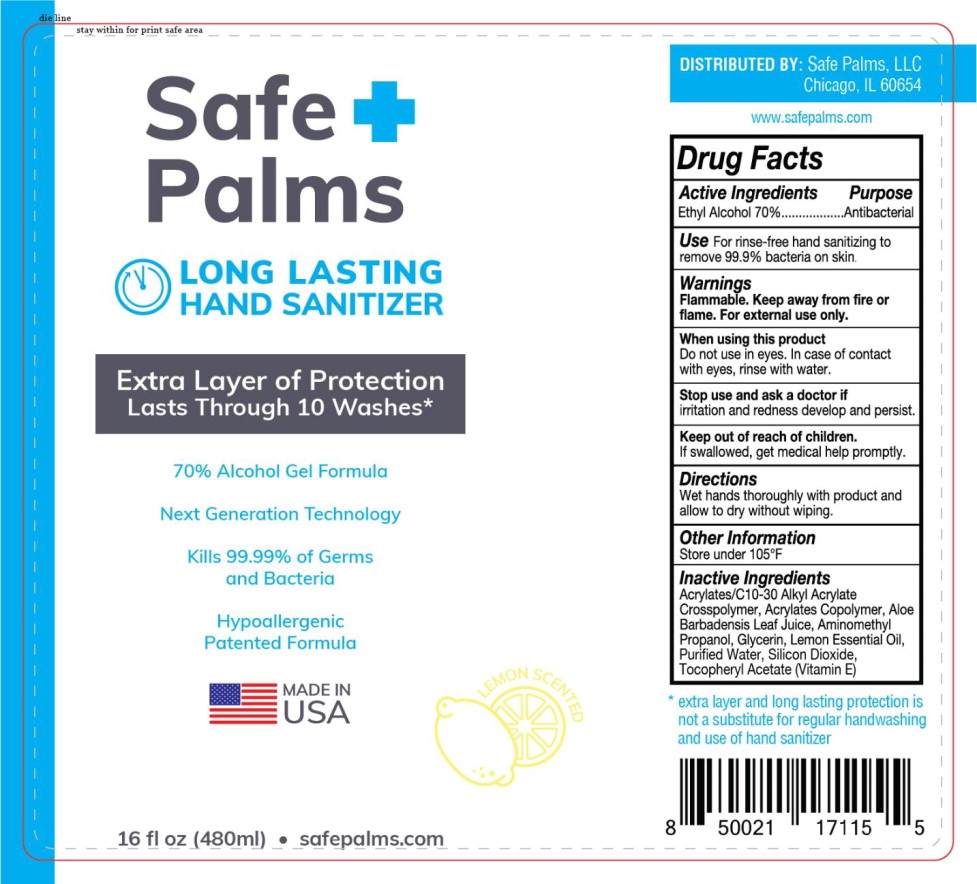 DRUG LABEL: Long Lasting Hand Sanitizer
NDC: 90117-104 | Form: GEL
Manufacturer: Safe Palms, LLC
Category: otc | Type: HUMAN OTC DRUG LABEL
Date: 20200825

ACTIVE INGREDIENTS: ALCOHOL 70 mL/100 mL
INACTIVE INGREDIENTS: CARBOMER INTERPOLYMER TYPE A (ALLYL SUCROSE CROSSLINKED); BUTYL ACRYLATE/METHYL METHACRYLATE/METHACRYLIC ACID COPOLYMER (18000 MW); ALOE VERA LEAF; AMINOMETHYLPROPANOL; GLYCERIN; WATER; SILICON DIOXIDE; .ALPHA.-TOCOPHEROL ACETATE; Lemon Oil

Drug Facts

Active Ingredients

Ethyl Alcohol 70%

Purpose

Antibacterial

Use

For rinse-free hand sanitizing to remove 99.9% bacteria on skin

Warnings

Flammable. Keep away from fire or flame. For external use only.

When using this product

Do not use in eyes. In case of contact with eyes, rinse with water.

Keep out of reach of children.

If swallowed, get medical help promptly.

Directions

Wet hands thoroughly with product and allow to dry without wiping.

Other Information

Store under 105°F

Inactive Ingredients

Acrylates/C10-30 Alkyl Acrylate Crosspolymer, Acrylates Copolymer, Aloe Barbadensis Leaf Juice, Aminomethyl Propanol, Glycerin, Lemon Essential Oil, Purified Water, Silicon Dioxide, Tocopheryl Acetate (Vitamin E)

PACKAGE LABEL

Safe +
Palms

LONG LASTING
HAND SANITIZER

Extra Layer of Protection

Lasts Through 10 Washes*

70% Alcohol Gel Formula

Next Generation Technology

Kills 99.99% of Germs
and Bacteria

Hypoallergenic
Patented Formula

MADE IN
USA

LEMON SCENTED

16 fl oz (480ml) • safepalms.com